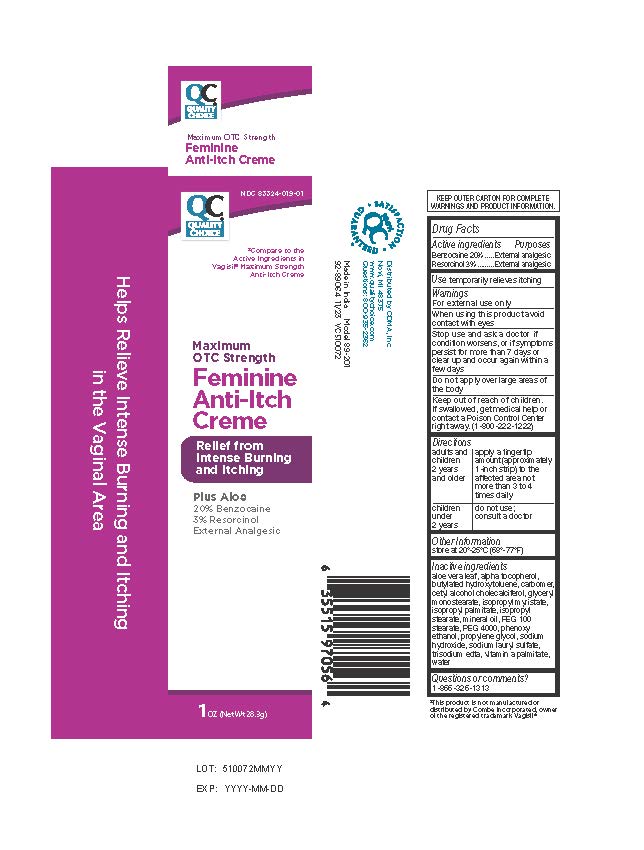 DRUG LABEL: Maximum OTC Strength Feminine Anti-Itch Creme
NDC: 83324-019 | Form: CREAM
Manufacturer: Quality Choice (CHAIN DRUG MARKETING ASSOCIATION)
Category: otc | Type: HUMAN OTC DRUG LABEL
Date: 20251229

ACTIVE INGREDIENTS: BENZOCAINE 5.67 g/28 g; RESORCINOL 0.85 g/28 g
INACTIVE INGREDIENTS: CARBOMER HOMOPOLYMER TYPE C (ALLYL PENTAERYTHRITOL CROSSLINKED); CETYL ALCOHOL; CHOLECALCIFEROL; GLYCERYL MONOSTEARATE; ISOPROPYL MYRISTATE; ISOPROPYL PALMITATE; ISOPROPYL STEARATE; BUTYLATED HYDROXYTOLUENE; POLYETHYLENE GLYCOL 4000; MINERAL OIL; PEG-100 STEARATE; PROPYLENE GLYCOL; WATER; ALOE VERA LEAF; VITAMIN A PALMITATE; SODIUM HYDROXIDE; SODIUM LAURYL SULFATE; ALPHA-TOCOPHEROL; EDETATE TRISODIUM; PHENOXYETHANOL

Quality Choice Maximum OTC Strength Feminine Anti-itch Creme

Drug Facts Active ingredients

Benzocaine 20%
Resorcinol 3%

Purpose

External analgesic

Keep out of reach of children

If swallowed, get medical help or contact a Poison Control Center right away. (1-800-222-1222)

Use

temporarily relieves itching

Warnings

For external use only

When using this product

avoid contact with the eyes

Stop use and ask a doctor if

condition worsens, or if symptoms persist for more than7 days or clear up and occur again within a few days

Do not apply Directions

Do not apply over large area of the body.

adults and children 12 years and older: apply a fingertip amount (approximately 1-inch strip) to the affected area not more than 3 to 4 times daily

children under 12 years: do not use; consult a doctor

Other Information

store at 20° -25° C (68° -77° F)

Inactive Ingredients

aloe vera leaf, alpha-tocopherol, butylated hydroxytoluene, carbomer, cetyl alcohol cholecalciferol, glyceryl monostearate,

isopropyl myristate, isopropyl palmitate, isopropyl stearate, mineral oil, PEG 100 stearate, PEG 4000, phenoxy ethanol, propylene glycol, sodium hydroxide, sodium lauryl sulfate, trisodium edta, vitamin A palmitate, water

Questions or comments?

1-866-326-1313